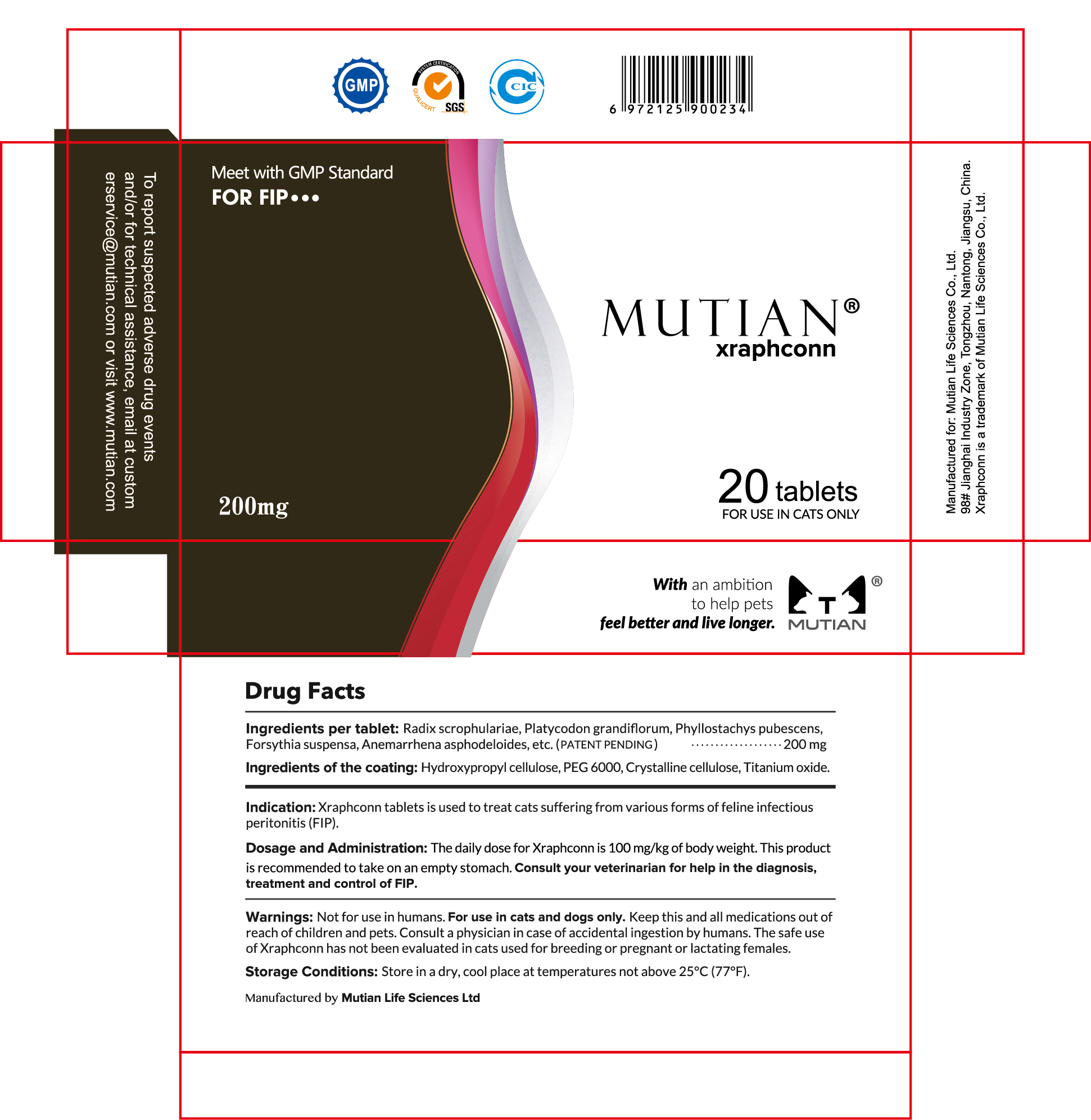 DRUG LABEL: MUTIAN Xraphconn for FIP
NDC: 73452-180 | Form: TABLET, COATED
Manufacturer: Nantong MUTIAN Biotechnology Co., Ltd
Category: animal | Type: OTC ANIMAL DRUG LABEL
Date: 20201017

ACTIVE INGREDIENTS: SCROPHULARIA NINGPOENSIS ROOT 70 mg/200 mg
INACTIVE INGREDIENTS: PLATYCODON GRANDIFLORUS ROOT 40 mg/200 mg; PHYLLOSTACHYS EDULIS STEM 30 mg/200 mg; FORSYTHIA SUSPENSA FRUIT 30 mg/200 mg; ANEMARRHENA ASPHODELOIDES ROOT 30 mg/200 mg

MuTian, Xraphconn, 200mg *20 tablets

Warnings

FOR USE IN CATS ONLY

Not for use in humans. For use in cats only. Keep this and all medications out of reach of children and pets. Consult a physician in case of accidental ingestion by humans. The safe use of Xraphconn has not been evaluated in cats used for breeding or pregnant or lactating females.

Indication

Xraphconn tablet is used to treat cats suffering from various forms of feline infectious peritonitis (FIP).

Dosage and Administration

The daily dose for Xraphconn is 100mg/kg of body weight. This product is recommended to take on an empty stomach. Consult your veterinarian for help in the diagnosis, treatment and control of FIP.

Active Ingredient

Radix scrophulariae 35%

Inactive Ingredients

Platycodon grandiflorum
Phyllostachys pubescens
Forsythia suspensa
Anemarrhena asphodeloides

KEEP OUT OF REACH OF CHILDREN

Keep this and all medications out of reach of children and pets.

Storage Conditions

Store in a dry, cool place at temperatures not above 25℃ (77℉).

Package Label - Principal Display Panel

Outer Package